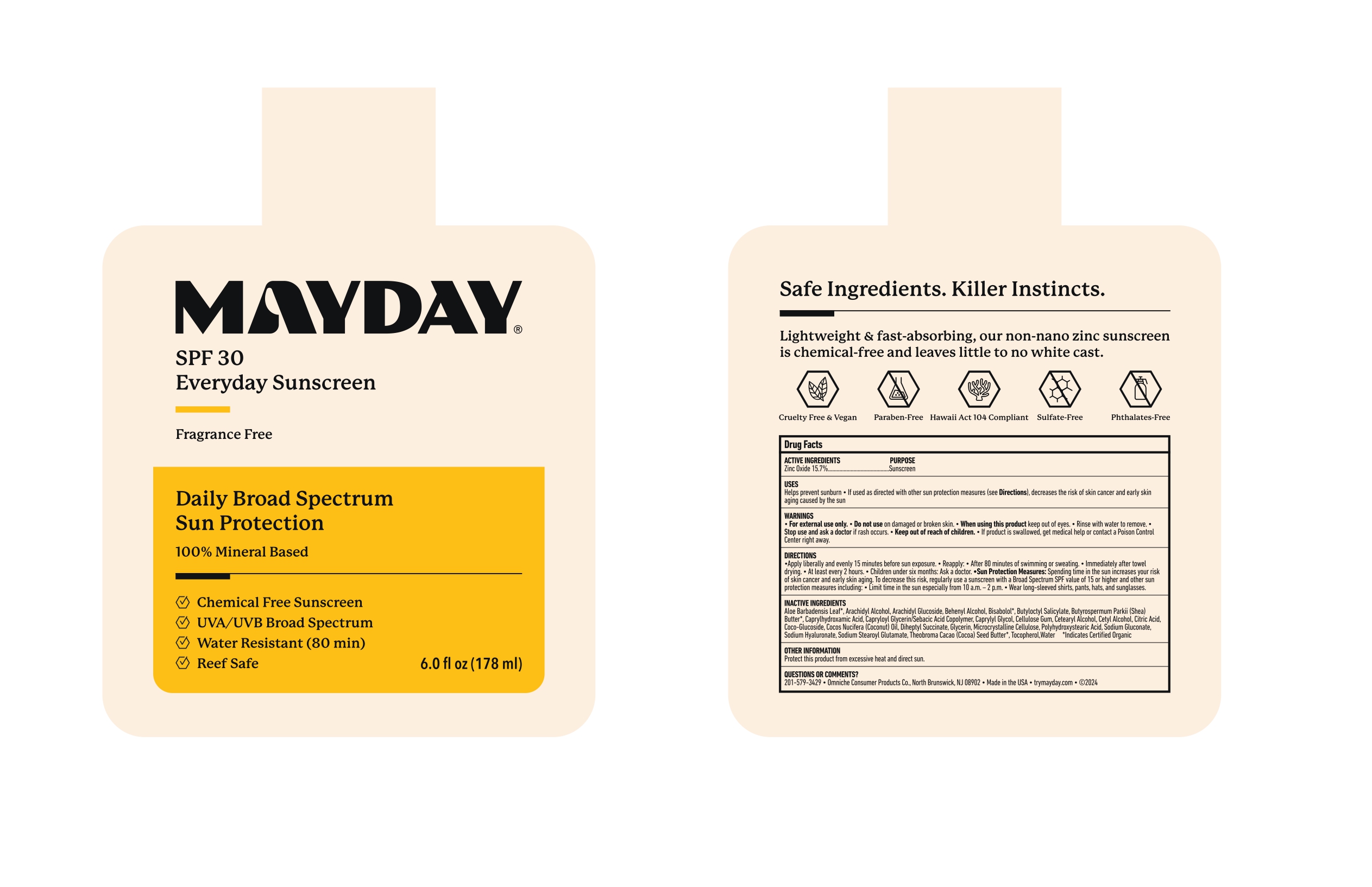 DRUG LABEL: MAYDAY Everyday Sunscreen SPF 30
NDC: 87045-157 | Form: LOTION
Manufacturer: Omniche Consumer Products Co.
Category: otc | Type: HUMAN OTC DRUG LABEL
Date: 20250904

ACTIVE INGREDIENTS: ZINC OXIDE 15.7 g/100 mL
INACTIVE INGREDIENTS: ALOE VERA LEAF; ARACHIDYL ALCOHOL; ARACHIDYL GLUCOSIDE; DOCOSANOL; LEVOMENOL; BUTYLOCTYL SALICYLATE; SHEA BUTTER; CAPRYLHYDROXAMIC ACID; CAPRYLOYL GLYCERIN/SEBACIC ACID COPOLYMER (2000 MPA.S); CAPRYLYL GLYCOL; CARBOXYMETHYLCELLULOSE SODIUM, UNSPECIFIED; CETOSTEARYL ALCOHOL; CETYL ALCOHOL; CITRIC ACID MONOHYDRATE; COCO-GLUCOSIDE; COCONUT OIL; DIHEPTYL SUCCINATE; GLYCERIN; MICROCRYSTALLINE CELLULOSE; POLYHYDROXYSTEARIC ACID (2300 MW); SODIUM GLUCONATE; HYALURONATE SODIUM; SODIUM STEAROYL GLUTAMATE; COCOA BUTTER; TOCOPHEROL; WATER

MAYDAY Everyday Sunscreen SPF 30

ACTIVE INGREDIENT

Zinc Oxide.........15.7%

PURPOSE

Sunscreen

USES

- Helps prevent sunburn
- if used as directed with other sun protection measures (see Directions), decreases the risk of skin cancer and early skin aging caused by the sun

WARNINGS

- For external use only

- Do not use on damaged or broken skin

- When using this product keep out of eyes. Rinse with water to remove.

- Stop use and ask a doctor if rash occurs

- Keep out of reach of children. if product is swallowed, get medical help or contact a Poison Control Center right away.

DIRECTIONS

- Apply liberally and evenly 15 minutes before sun exposure.
- Reapply: After 80 minutes of swimming or sweating
- Immediately after towel drying
- atleast every 2 hours.
- Children under six months: Ask a doctor
- Sun Protection Measures: Spending time in the sun increases your risk of skin cancer and early skin aging. To decrease this risk, regularly use a sunscreen with a Broad Spectrum SPF value of 15 or higher and other sun protection measures including Limit time in the sun especially from 10 a.m- 2 p.m. Wear long-sleeved shirts, pants hats, and sunglasses.

INACTIVE INGREDIENTS

Aloe Barbadensis Leaf*, Arachidyl Alcohol, Arachidyl Glucoside, Behenyl Alcohol, Bisabolol*, Butyloctyl Salicylate, Butyrospermum Parkii (Shea) Butter*, Caprylhydroxamic Acid, Capryloyl Glycerin/Sebacic Acid Copolymer, Caprylyl Glycol, Cellulose Gum, Cetearyl Alcohol, Cetyl Alcohol, Citric Acid, Coco-Glucoside, Cocos Nucifera (Coconut) oil, Diheptyl Succinate, Glycerin, Microcrystalline Cellulose, Polyhydroxystearic Acid, Sodium Gluconate, Sodium Hyaluronate, Sodium Stearoyl Glutamate, Theobroma Cacao (Cocoa) Seed Butter*, Tocopherol, Water *Indicates Certified Organic

OTHER INFORMATION

Protect this product from excessive heat and direct sun

QUESTIONS OR COMMENTS ?

201-579-3429

- Omniche Consumer Products Co., North Brunswick, NJ 08902
- Made in USA
- trymayday.com